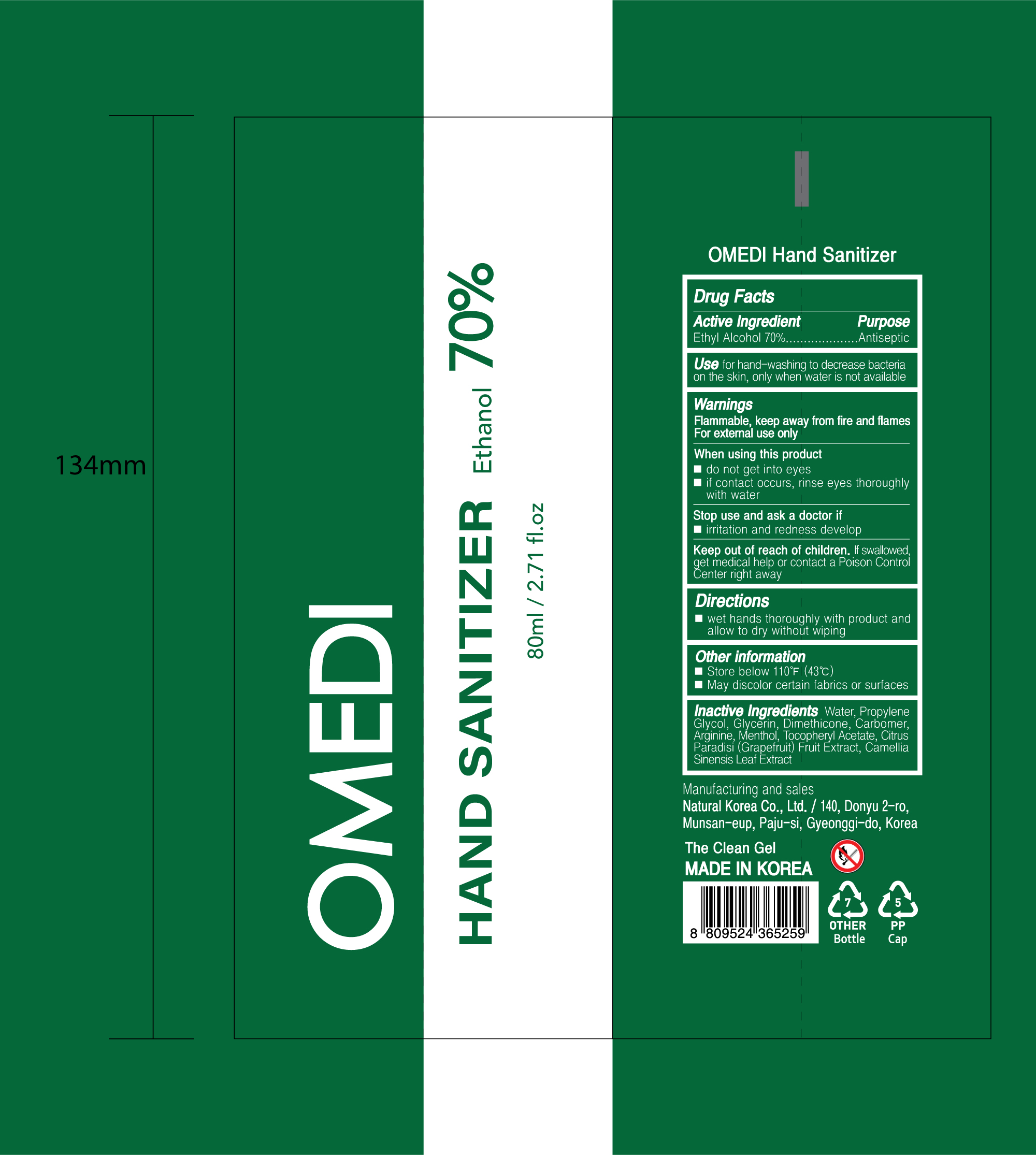 DRUG LABEL: OMEDI HAND SANITIZER
NDC: 74646-0080 | Form: GEL
Manufacturer: Natural Korea Co., Ltd.
Category: otc | Type: HUMAN OTC DRUG LABEL
Date: 20200420

ACTIVE INGREDIENTS: ALCOHOL 56 mL/80 mL
INACTIVE INGREDIENTS: ALPHA-TOCOPHEROL ACETATE; MENTHOL; PROPYLENE GLYCOL; GLYCERIN; DIMETHICONE; GREEN TEA LEAF; WATER; CARBOMER HOMOPOLYMER, UNSPECIFIED TYPE; ARGININE; GRAPEFRUIT

[OMEDI HAND SANITIZER 80 ml : 74646-0080-1